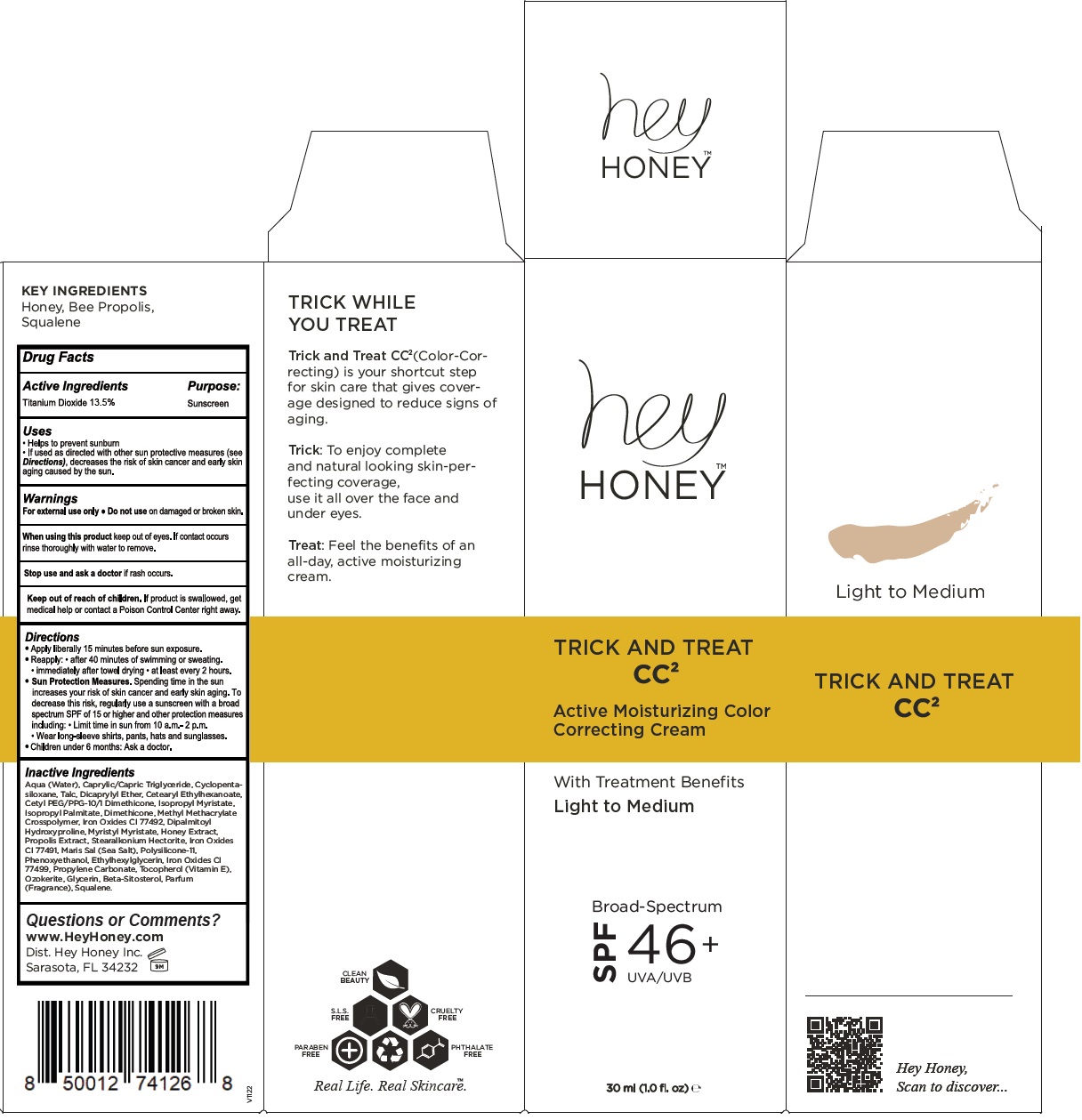 DRUG LABEL: TRICK AND TREAT CC2 - Active Moisturizing Color Correcting Broad-Spectrum SPF 46 Plus
NDC: 84192-123 | Form: CREAM
Manufacturer: HEY HONEY INC.
Category: otc | Type: HUMAN OTC DRUG LABEL
Date: 20260105

ACTIVE INGREDIENTS: TITANIUM DIOXIDE 13.5 g/100 mL
INACTIVE INGREDIENTS: WATER; MEDIUM-CHAIN TRIGLYCERIDES; CYCLOMETHICONE 5; TALC; DICAPRYLYL ETHER; CETEARYL ETHYLHEXANOATE; CETYL PEG/PPG-10/1 DIMETHICONE (HLB 5); ISOPROPYL MYRISTATE; ISOPROPYL PALMITATE; DIMETHICONE; METHYL METHACRYLATE/GLYCOL DIMETHACRYLATE CROSSPOLYMER; FERRIC OXIDE YELLOW; DIPALMITOYL HYDROXYPROLINE; MYRISTYL MYRISTATE; HONEY; PROPOLIS WAX; STEARALKONIUM HECTORITE; FERRIC OXIDE RED; SEA SALT; DIMETHICONE/VINYL DIMETHICONE CROSSPOLYMER (SOFT PARTICLE); PHENOXYETHANOL; ETHYLHEXYLGLYCERIN; FERROSOFERRIC OXIDE; PROPYLENE CARBONATE; TOCOPHEROL; CERESIN; GLYCERIN; .BETA.-SITOSTEROL; SQUALENE

hey HONEY™ TRICK AND TREAT CC² Active Moisturizing Color Correcting Cream

Active Ingredients

Titanium Dioxide 13.5%

Purpose:

Sunscreen

Uses

• Helps to prevent sunburn.
• If used as directed with other sun protective measures (see Directions), decreases the risk of skin cancer and early skin aging caused by the sun.

Warnings

For external use only • Do not use on damaged or broken skin.

When using this product keep out of eyes. If contact occurs rinse thoroughly with water to remove.

Stop use and ask a doctor if rash occurs.

Keep out of reach of children. If product is swallowed, get medical help or contact a Poison Control Center right away.

Directions

• Apply liberally 15 minutes before sun exposure.
• Reapply: • after 40 minutes of swimming or sweating. • immediately after towel drying • at least every 2 hours.
• Sun Protection Measures. Spending time in the sun increases your risk of skin cancer and early skin aging. To decrease this risk, regularly use a sunscreen with a broad spectrum SPF of 15 or higher and other protection measures including: • Limit time in sun from 10 a.m.- 2 p.m. • Wear long-sleeve shirts, pants, hats and sunglasses.
• Children under 6 months: Ask a doctor.

Inactive Ingredients

Aqua (Water), Caprylic/Capric Triglyceride, Cyclopentasiloxane, Talc, Dicaprylyl Ether, Cetearyl Ethylhexanoate, Cetyl PEG/PPG-10/1 Dimethicone, Isopropyl Myristate, Isopropyl Palmitate, Dimethicone, Methyl Methacrylate Crosspolymer, Iron Oxides CI 77492, Dipalmitoyl Hydroxyproline, Myristyl Myristate, Honey Extract, Propolis Extract, Stearalkonium Hectorite, Iron Oxides CI 77491, Maris Sal (Sea Salt), Polysilicone-11, Phenoxyethanol, Ethylhexylglycerin, Iron Oxides CI 77499, Propylene Carbonate, Tocopherol (Vitamin E), Ozokerite, Glycerin, Beta-Sitosterol, Parfum (Fragrance), Squalene.

Questions or Comments?

www.HeyHoney.com

Dist. Hey Honey Inc.
Sarasota, FL 34232

With Treatment Benefits

Light to Medium

Broad-Spectrum SPF 46+
UVA/UVB

KEY INGREDIENTS
Honey, Bee Propolis, Squalene

TRICK WHILE YOU TREAT

Trick and Treat CC^2 (Color-Correcting) is your shortcut step for skin care that gives coverage designed to reduce signs of aging.

Trick: To enjoy complete and natural looking skin-perfecting coverage, use it all over the face and under eyes.

Treat: Feel the benefits of an all-day, active moisturizing cream.

CLEAN BEAUTY
S.L.S FREE
CRUELTY FREE
PARABEN FREE
PHTHALATE FREE

Real Life. Real SkincareTM.